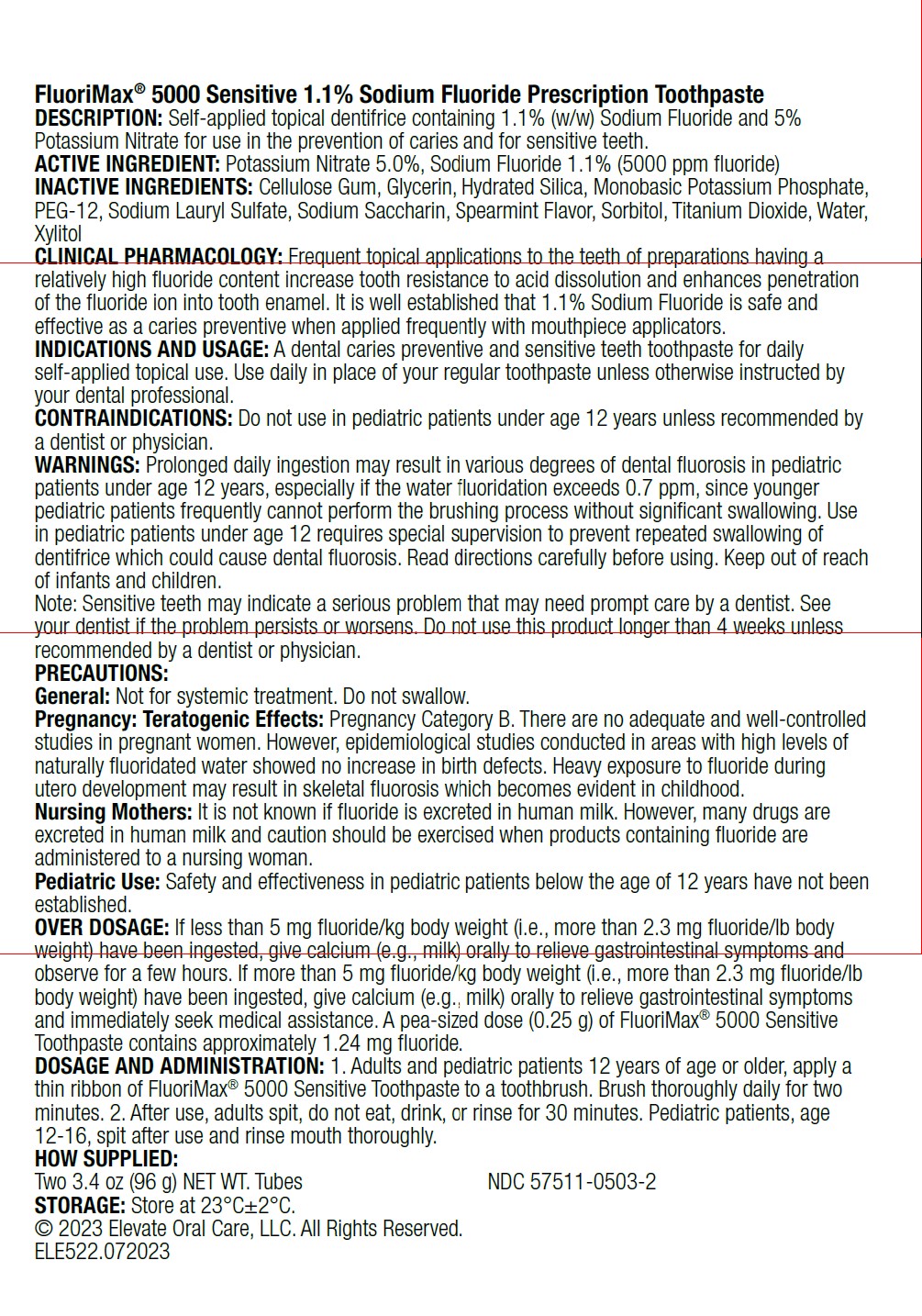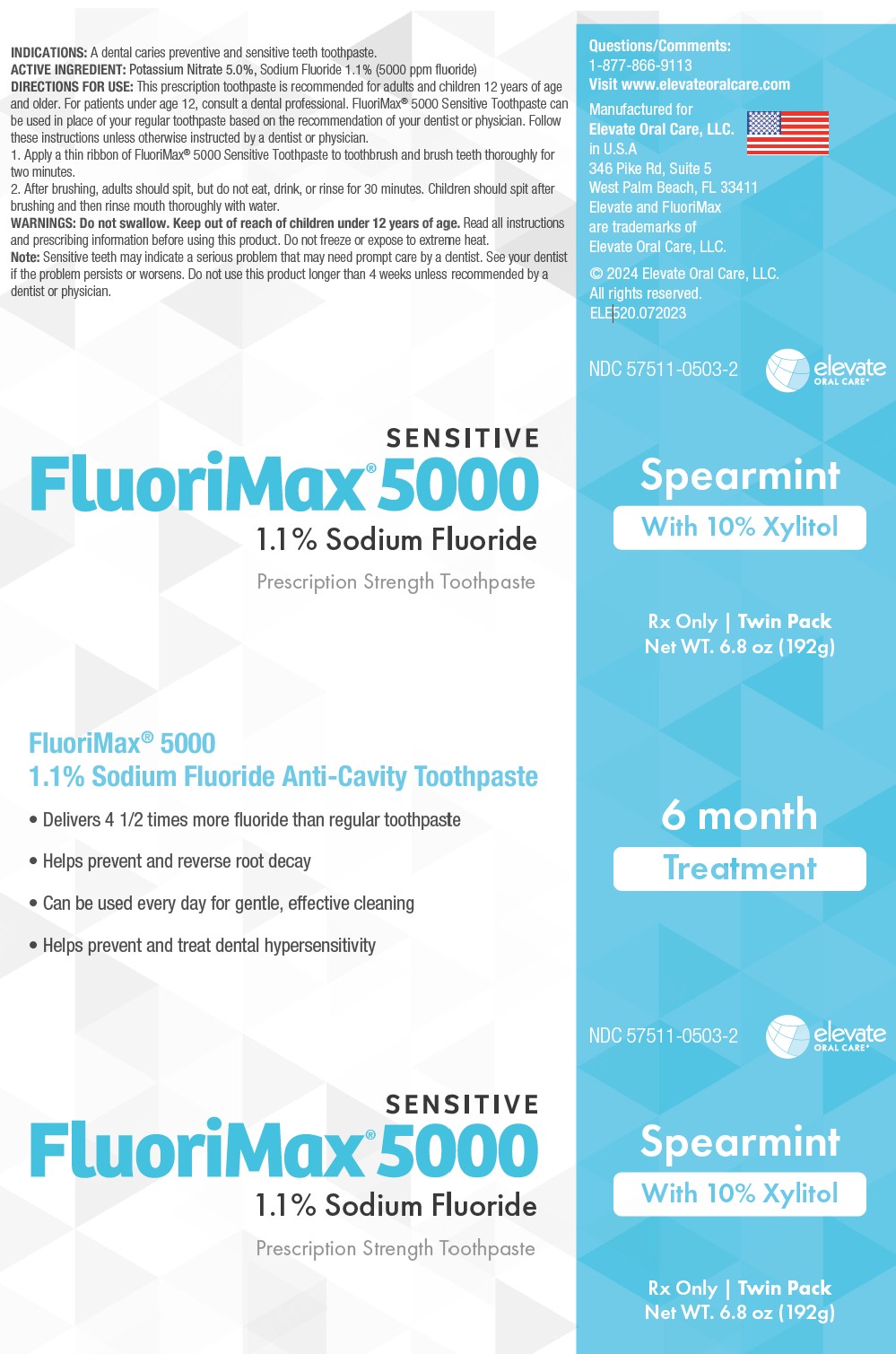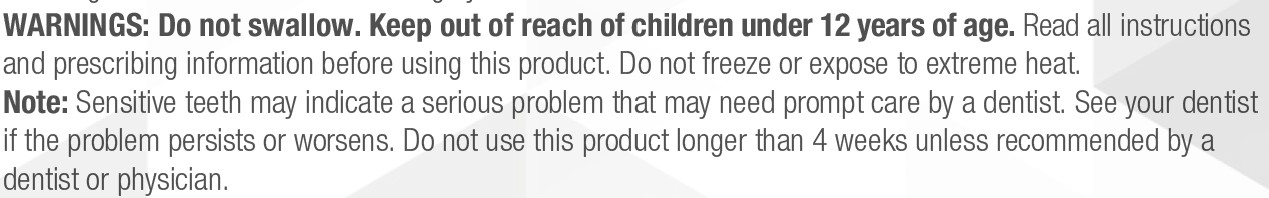 DRUG LABEL: FluoriMax 5000 Sensitive
NDC: 57511-0503 | Form: PASTE, DENTIFRICE
Manufacturer: Elevate Oral Care
Category: prescription | Type: HUMAN PRESCRIPTION DRUG LABEL
Date: 20250919

ACTIVE INGREDIENTS: SODIUM FLUORIDE 1.1 g/100 g; POTASSIUM NITRATE 5 g/100 g
INACTIVE INGREDIENTS: SACCHARIN; GLYCERIN; HYDRATED SILICA; XYLITOL; POTASSIUM PHOSPHATE, MONOBASIC; WATER; SORBITOL

FluoriMax 5000 1.1% Sodium Fluoride & 5% Potassium Nitrate Toothpaste Spearmint